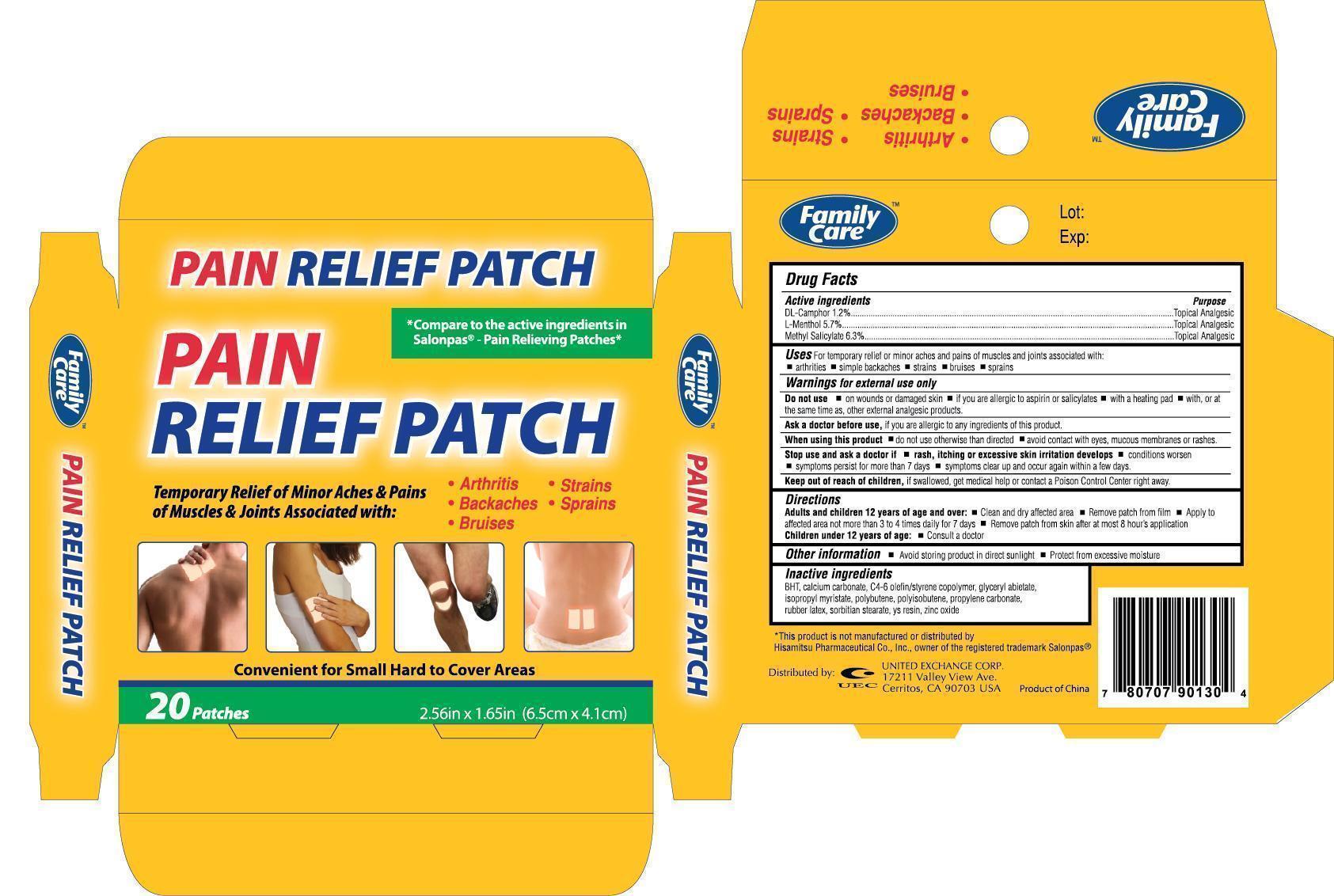 DRUG LABEL: Family Care Pain Relief
NDC: 65923-385 | Form: PATCH
Manufacturer: United Exchange Corp.
Category: otc | Type: HUMAN OTC DRUG LABEL
Date: 20131126

ACTIVE INGREDIENTS: CAMPHOR (SYNTHETIC) 1.2 g/100 g; LEVOMENTHOL 5.7 g/100 g; METHYL SALICYLATE 6.3 g/100 g
INACTIVE INGREDIENTS: BUTYLATED HYDROXYTOLUENE; CALCIUM CARBONATE; STYRENE; GLATIRAMER ACETATE; ISOPROPYL MYRISTATE; POLYISOBUTYLENE (1000 MW); POLYBUTENE (1400 MW); PROPYLENE CARBONATE; SORBITAN MONOSTEARATE; ZINC OXIDE

Active Ingredients Purpose

DL-Camphor 1.2%....................................................Topical Analgesic

L-Menthol 5.7%........................................................Topical Analgesic
Methylsalicylate 6.3%................................................Topical Analgesic

Uses

For temporary relief of minor aches and pains of muscles and joints associated with:

- arthritis
- simple backaches
- strains
- bruises
- sprains

Warnings

For external use only

Do not use

- on wounds or damaged skin
- if you are allergic to aspirin or salicylates
- with a heating pad
- with, or at the same time as, other external analgesic products

Ask a doctor before use, if you are allergic to any ingredients in this product

When using this product

- do not use otherwise than directed
- avoid contact with the eyes, mucous membranes or rashes

Stop use and ask a doctore if

- rash, itching or excessive skin irritation develops
- conditions worsen
- symptoms persist for more than 7 days
- symptoms clear up and occur again within a few days

Keep out of reach of children, if swallowed, get medical help or contact a Poision Control Center right away

Directions

Aduts and children 12 years of age and over:

- clean and dry affected area
- remove patch from film
- apply to affected area no more than 3 to 4 times daily for 7 days
- remove patch from skin after at most 8 hours of application

Children under 12 years of age:

- consult a doctor

Other Information

- avoid storing product in direct sunlight
- protect from excessive moisture

Inactive Ingredients

BHT, calcium carbonate, C4-6 oletin / styrene copolymer, glycerol abietate, isopropyl myristate, polybutene, polyisobutene, propylene carbonate, rubber latex, sorbitian stearate, ys resin, zinc oxide

DOSAGE AND ADMINISTRATION

DISTRIBUTED BY:

UNITED EXCHANGE CORP.

17211 VALLEY VIEW AVE.

CERRITOS, CA 90703